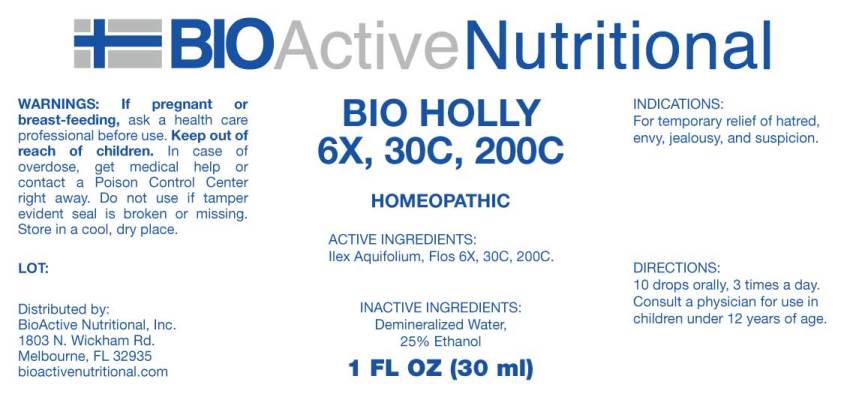 DRUG LABEL: Bio Holly
NDC: 43857-0364 | Form: LIQUID
Manufacturer: BioActive Nutritional, Inc.
Category: homeopathic | Type: HUMAN OTC DRUG LABEL
Date: 20230606

ACTIVE INGREDIENTS: ILEX AQUIFOLIUM FRUITING TOP 6 [hp_X]/1 mL
INACTIVE INGREDIENTS: WATER; ALCOHOL

DRUG FACTS:

ACTIVE INGREDIENTS:

Ilex Aquifolium (Holly), Flos 6X, 30C, 200C.

INDICATIONS:

For temporary relief of hatred, envy, jealousy, and suspicion.

WARNINGS:

If pregnant or breast-feeding, ask a health care professional before use.

Keep out of reach of children. In case of overdose, get medical help or contact a Poison Control Center right away.

Do not use if tamper evident seal is broken or missing.

Store in a cool, dry place.

Keep out of reach of children. In case of overdose, get medical help or contact a Poison Control Center right away.

DIRECTIONS:

10 drops orally, 3 times a day. Consult a physician for use in children under 12 years of age.

INDICATIONS:

For temporary relief of hatred, envy, jealousy, and suspicion.

INACTIVE INGREDIENTS:

Demineralized Water, 25% Ethanol

QUESTIONS:

Distributed by:

BIOACTIVE NUTRITIONAL

Melbourne, FL 32935

For Nutritional Information Write:

BioActive Nutritional, Inc.

1803 N. Wickham Rd.

Melbourne, FL 32935

PACKAGE LABEL DISPLAY:

BioActive Homeopathic

BIO HOLLY 6X, 30C, 200C

1 FL OZ (30 ML)